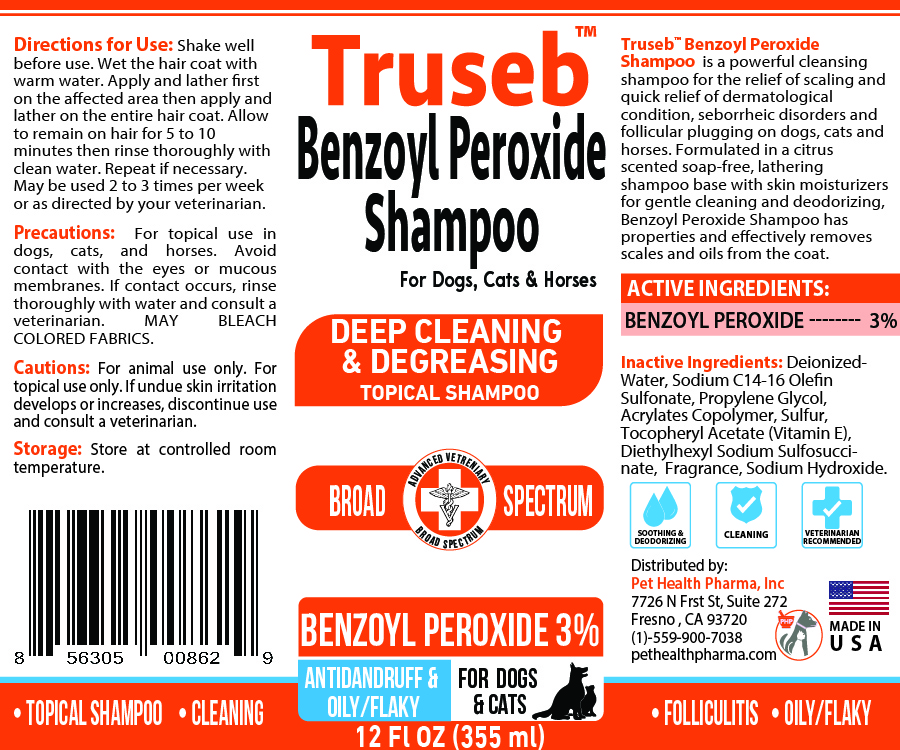 DRUG LABEL: Benzoyl Peroxide 3%
NDC: 86176-105 | Form: SHAMPOO
Manufacturer: Pet Health Pharma, LLC
Category: animal | Type: OTC ANIMAL DRUG LABEL
Date: 20250819

ACTIVE INGREDIENTS: BENZOYL PEROXIDE 3 g/100 mL
INACTIVE INGREDIENTS: WATER; SODIUM C14-16 OLEFIN SULFONATE; Propylene Glycol; ACRYLATES CROSSPOLYMER-4; Sulfur; ALPHA-TOCOPHEROL ACETATE; Diethylhexyl Sodium Sulfosuccinate; Sodium Hydroxide

Truseb Benzoyl Peroxide 3% Shampoo For Cats, Dogs and Horses

ACTIVE INGREDIENT

Benzoyl Peroxide 3%

INACTIVE INGREDIENTS:

Water, Sodium C14-16 Olefin Sulfonate, Propylene Glycol, Acrylates Copolymer, Sulfur, Tocopheryl Acetate (Vitamin E), Diethylhexyl Sodium Sulfosuccinate, Fragrance, Sodium Hydroxide.

INDICATIONS & USAGE:

Benzoyl Peroxide Shampoo is a powerful cleansing shampoo for the relief of scaling and quick relief of dermatological condition, seborrheic disorders and follicular plugging on dogs, cats and horses. Formulated in a citrus scented soap-free, lathering shampoo base with skin moisturizers for gentle cleaning and deodorizing, Benzoyl Peroxide Shampoo has properties and effectively removes scales and oils from the coat.

DIRECTIONS FOR USE:

Shake well before use. Wet the hair coat with warm water. Apply and lather first on the affected area then apply and lather on the entire hair coat. Allow to remain on hair for 5 to 10 minutes then rinse thoroughly with clean water. Repeat if necessary. May be used 2 to 3 times per week or as directed by your veterinarian.

PRECAUTIONS:

For animal use only. For topical use only. Avoid contact with eyes or mucous membranes. If undue skin irritation develops or increases, discontinue use and consult your veterinarian. In case of contact, flush eyes with water and seek medical attention if undue irritation persists. Keep out of the reach of children.

STORAGE:

Store at controlled room temperature.

SPL UNCLASSIFIED SECTION

For Dogs, Cats & Horses

DEEP CLEANING & DEGREASING TOPICAL SHAMPOO

PASSION FRUIT SCENT

• FOLLICULITIS • OILY/FLAKY

• Topical shampoo • Cleaning

AntiDandruff

ADVANCED VETERINARY FORMULA
Broad Spectrum
Made In USA

Distributed by:
Pet Health Pharma, Inc
7726 N Frst St, Suite 272
Fresno , CA 93720
(1)-559-900-7038
pethealthpharma.com